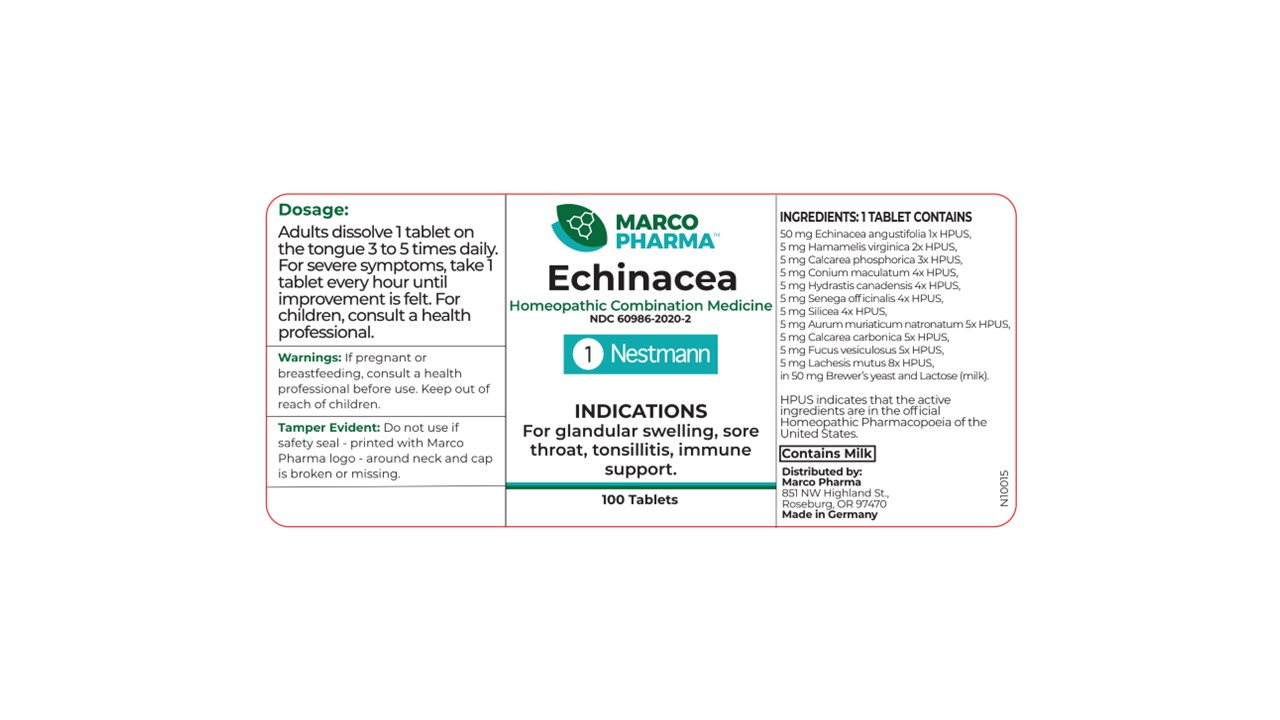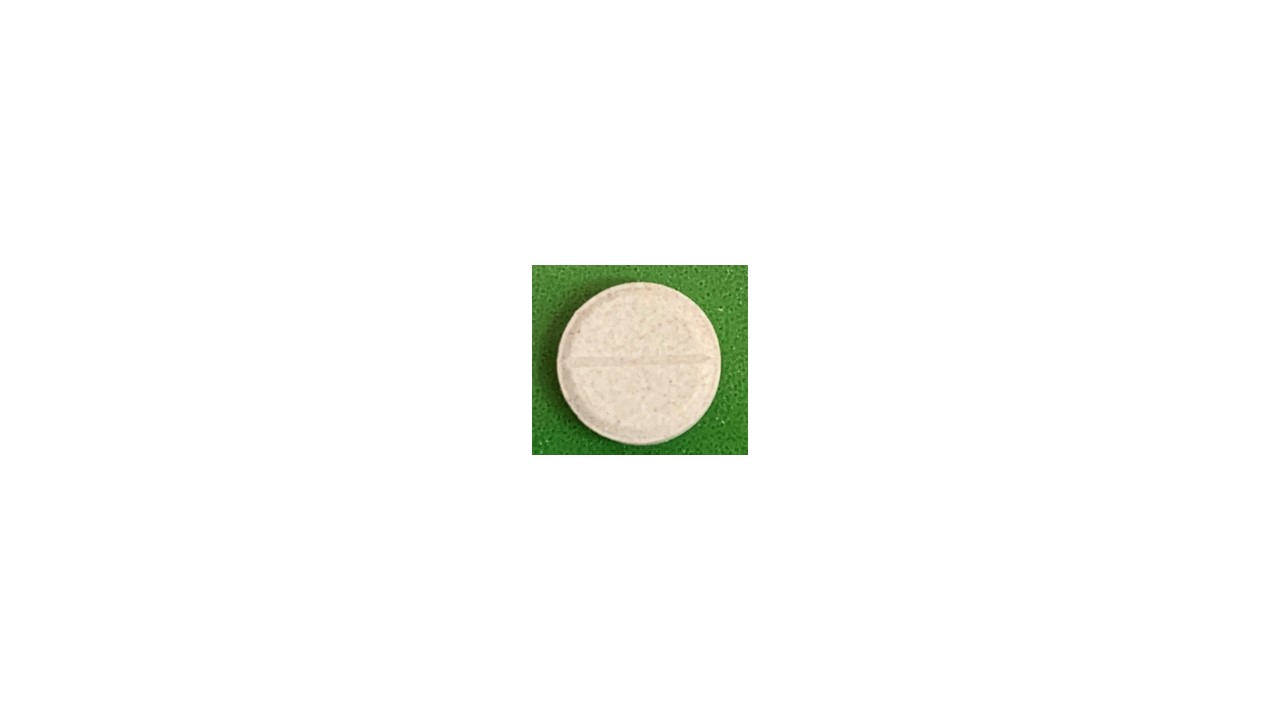 DRUG LABEL: ECHINACEA
NDC: 60986-2020 | Form: TABLET, ORALLY DISINTEGRATING
Manufacturer: Marco Pharma International LLC.
Category: homeopathic | Type: HUMAN OTC DRUG LABEL
Date: 20260112

ACTIVE INGREDIENTS: ECHINACEA ANGUSTIFOLIA 1 [hp_X]/1 1; HAMAMELIS VIRGINIANA ROOT BARK/STEM BARK 2 [hp_X]/1 1; TRIBASIC CALCIUM PHOSPHATE 3 [hp_X]/1 1; GOLDENSEAL 4 [hp_X]/1 1; POLYGALA SENEGA ROOT 4 [hp_X]/1 1; SILICON DIOXIDE 4 [hp_X]/1 1; CONIUM MACULATUM FLOWERING TOP 4 [hp_X]/1 1; SODIUM TETRACHLOROAURATE 5 [hp_X]/1 1; OYSTER SHELL CALCIUM CARBONATE, CRUDE 5 [hp_X]/1 1; FUCUS VESICULOSUS 5 [hp_X]/1 1; LACHESIS MUTA VENOM 8 [hp_X]/1 1
INACTIVE INGREDIENTS: LACTOSE; SACCHAROMYCES CEREVISIAE

Drug Facts

Active Ingredients

Coneflower 1XHPUS

Witch Hazel 2XHPUS

Tribasic calcium phosphate 3XHPUS

Goldenseal 4XHPUS

Milkwort 4XHPUS

Silicon dioxide 4XHPUS

Poison Hemlock 4XHPUS

Sodium tetrachloroaurate 5XHPUS

Impure Calcium Carbonate 5XHPUS

Bladder-wrack 5XHPUS

Bushmaster viper venom 8XHPUS

The letters HPUS indicates that the components in this product are officially monographed in the Homeopathic Pharmacopoeia of United Sates.

Purpose

FOR TEMPORARY RELIEF OF SORE THROATS AND LYMPHATIC INFLAMMATION.

Keep out of reach of children.

Dosage

Adults take 1 tablet three times daily, dissolving on the tongue. For severe symptoms, take one tablet every hour until improvement is felt. Children receive 1/2 tablet as above.

Warnings

If pregnant or breast-feeding, consult a health professional before use.

DOSAGE AND ADMINISTRATION

(Read Suggested Use Section)

Inactive Ingredients

Faex Med. and Lactose